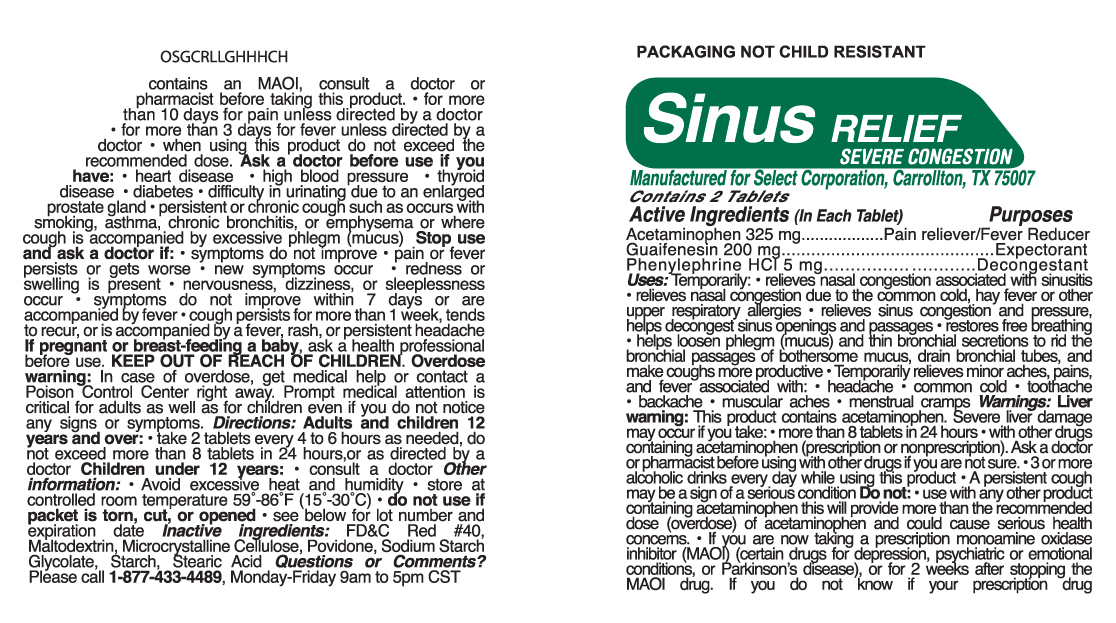 DRUG LABEL: Sinus Relief Severe Congestion
                
                
                
NDC: 52904-455 | Form: TABLET
Manufacturer: Select Corporation
Category: otc | Type: HUMAN OTC DRUG LABEL
Date: 20121015

ACTIVE INGREDIENTS: ACETAMINOPHEN 325 mg/1 1; PHENYLEPHRINE HYDROCHLORIDE 5 mg/1 1; GUAIFENESIN 200 mg/1 1
INACTIVE INGREDIENTS: STARCH, CORN; POVIDONE K30; STEARIC ACID; CELLULOSE, MICROCRYSTALLINE; SODIUM STARCH GLYCOLATE TYPE A POTATO; FD&C RED NO. 40; MALTODEXTRIN

ACTIVE INGREDIENT

Active Ingredients Purpose

Acetaminophen 325 mg.......................Pain Reliever/Fever Reducer
Guaifenesin 200 mg.............................Expectorant
Phenylephrine HCl 5 mg.............................Nasal Decongestant

PURPOSE

Pain Reliever, Fever Reducer, Expectorant, Nasal Decongestant

DOSAGE

Directions: Adults and children 12
years and over: • take 2 tablets every 4 to 6 hours as needed, do
not exceed more than 8 tablets in 24 hours,or as directed by a
doctor Children under 12 years: • consult a doctor

INDICATIONS

Uses: Temporarily:

• relieves nasal congestion associated with sinusitis
• relieves nasal congestion due to the common cold, hay fever or other upper respiratory allergies • relieves sinus congestion and pressure, helps decongest sinus openings and passages • restores free breathing
• helps loosen phlegm (mucus) and thin bronchial secretions to rid the bronchial passages of bothersome mucus, drain bronchial tubes, and make coughs more productive

• Temporarily relieves minor aches, pains, and fever associated with:

• headache

• common cold

• toothache

• backache

• muscular aches

• menstrual cramps

WARNINGS

Liver warning: This product contains acetaminophen. Severe liver damage may occur if you take: • more than 8 tablets in 24 hours • with other drugs containing acetaminophen (prescription or nonprescription). Ask a doctor or pharmacist before using with other drugs if you are not sure. • 3 or more alcoholic drinks every day while using this product • A persistent cough may be a sign of a serious condition

Do not: • use with any other product containing acetaminophen this will provide more than the recommended
dose (overdose) of acetaminophen and could cause serious health concerns. • If you are now taking a prescription monoamine oxidase
inhibitor (MAOI) (certain drugs for depression, psychiatric or emotional conditions, or Parkinson’s disease), or for 2 weeks after stopping the
MAOI drug. If you do not know if your prescription drug contains an MAOI, ask a doctor or pharmacist before taking this product. • for more
than 10 days for pain unless directed by a doctor • for more than 3 days for fever unless directed by a
doctor • when using this product do not exceed the recommended dose. Ask a doctor before use if you
have: • heart disease • high blood pressure • thyroid disease • diabetes • difficulty in urinating due to an enlarged
prostate gland • persistent or chronic cough such as occurs with smoking, asthma, chronic bronchitis, or emphysema or where
cough is accompanied by excessive phlegm (mucus)

Stop use and ask a doctor if: • symptoms do not improve • pain or fever persists or gets worse • new symptoms occur • redness or
swelling is present • nervousness, dizziness, or sleeplessness occur • symptoms do not improve within 7 days or are
accompanied by fever • cough persists for more than 1 week, tends to recur, or is accompanied by a fever, rash, or persistent headache

PREGNANCY

If pregnant or breast-feeding baby, ask a health professional
before use.

KEEP OUT OF REACH OF CHILDREN.

INACTIVE INGREDIENT

Inactive ingredients: FDC Red 40,
Maltodextrin, Microcrystalline Cellulose, Povidone, Sodium Starch
Glycolate, Starch, Stearic Acid

PACKAGE LABEL

MM1